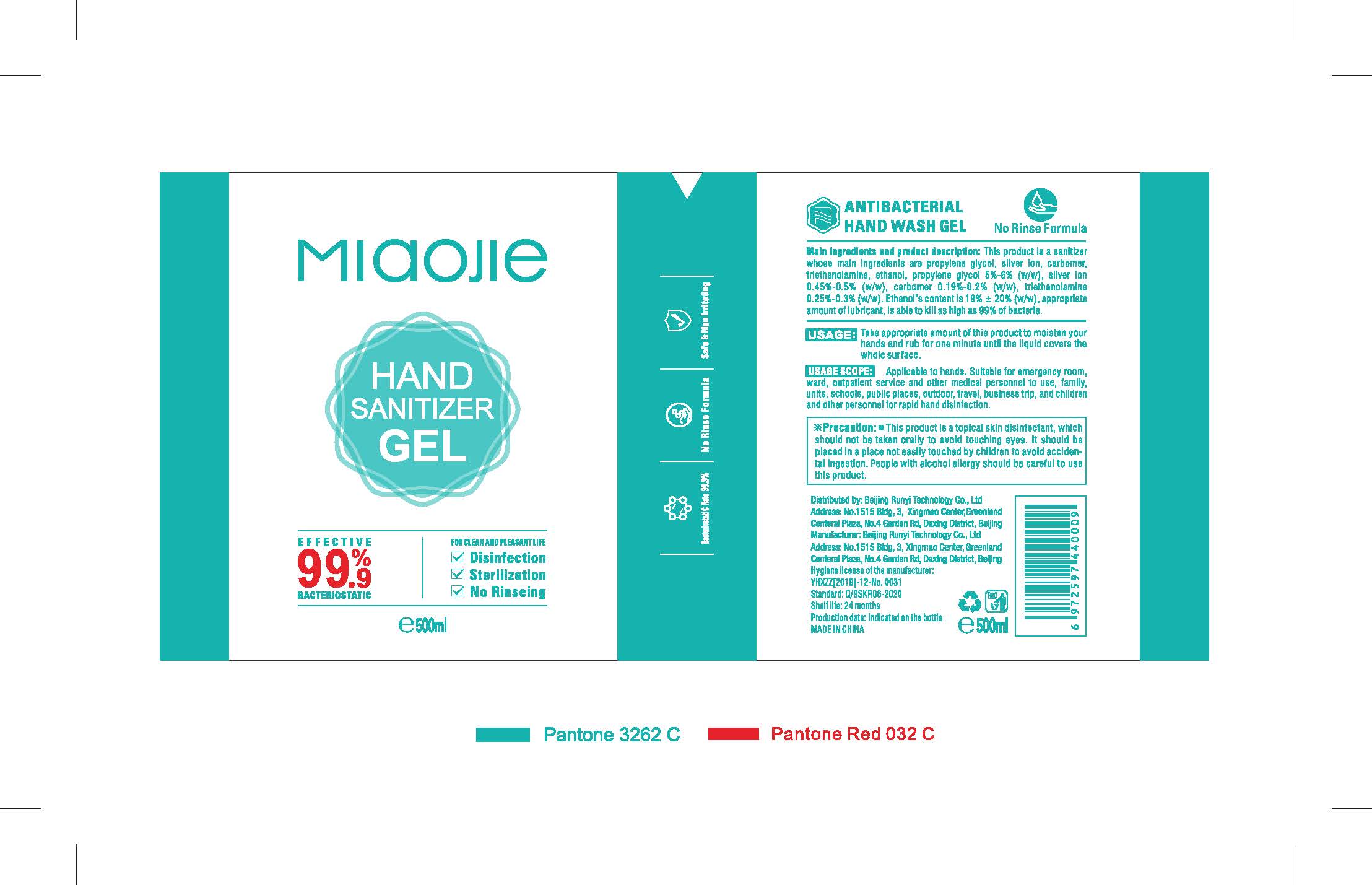 DRUG LABEL: RUNYI MIAOJIE Hand sanitizer
NDC: 41500-002 | Form: LIQUID
Manufacturer: Beijing Runyi Technology Co., Ltd
Category: otc | Type: HUMAN OTC DRUG LABEL
Date: 20200512

ACTIVE INGREDIENTS: ALCOHOL 95 mL/500 mL; CARBOMER HOMOPOLYMER, UNSPECIFIED TYPE 0.95 mg/500 mL; SILVER CATION 2.5 mg/500 mL; PROPYLENE GLYCOL 25 mg/500 mL; TROLAMINE 1.5 mg/500 mL
INACTIVE INGREDIENTS: WATER

DOSAGE AND ADMINISTRATION

Colorless transparent gel.

WARNINGS

This product is a topical skin disinfectant, which should not be taken orally to avoid touching eyes. It should be placed in a place not easily touched by children to avoid acciden-tal ingestion. People with alcohol alrgy should be careful to use this product.

INACTIVE INGREDIENT

Water

INDICATIONS AND USAGE

Take appropriate amount of this product to moisten your hands and rub for one minute until the liquid covers the whole surface.

KEEP OUT OF REACH OF CHILDREN

It should be placed in a place not easily touched by children to avoid acciden-tal ingestion.

PURPOSE

Disinfection
Sterilization
No Rinseing

ACTIVE INGREDIENT

propylene glycol, silver ion, carbomer, triethanolamine, ethanol